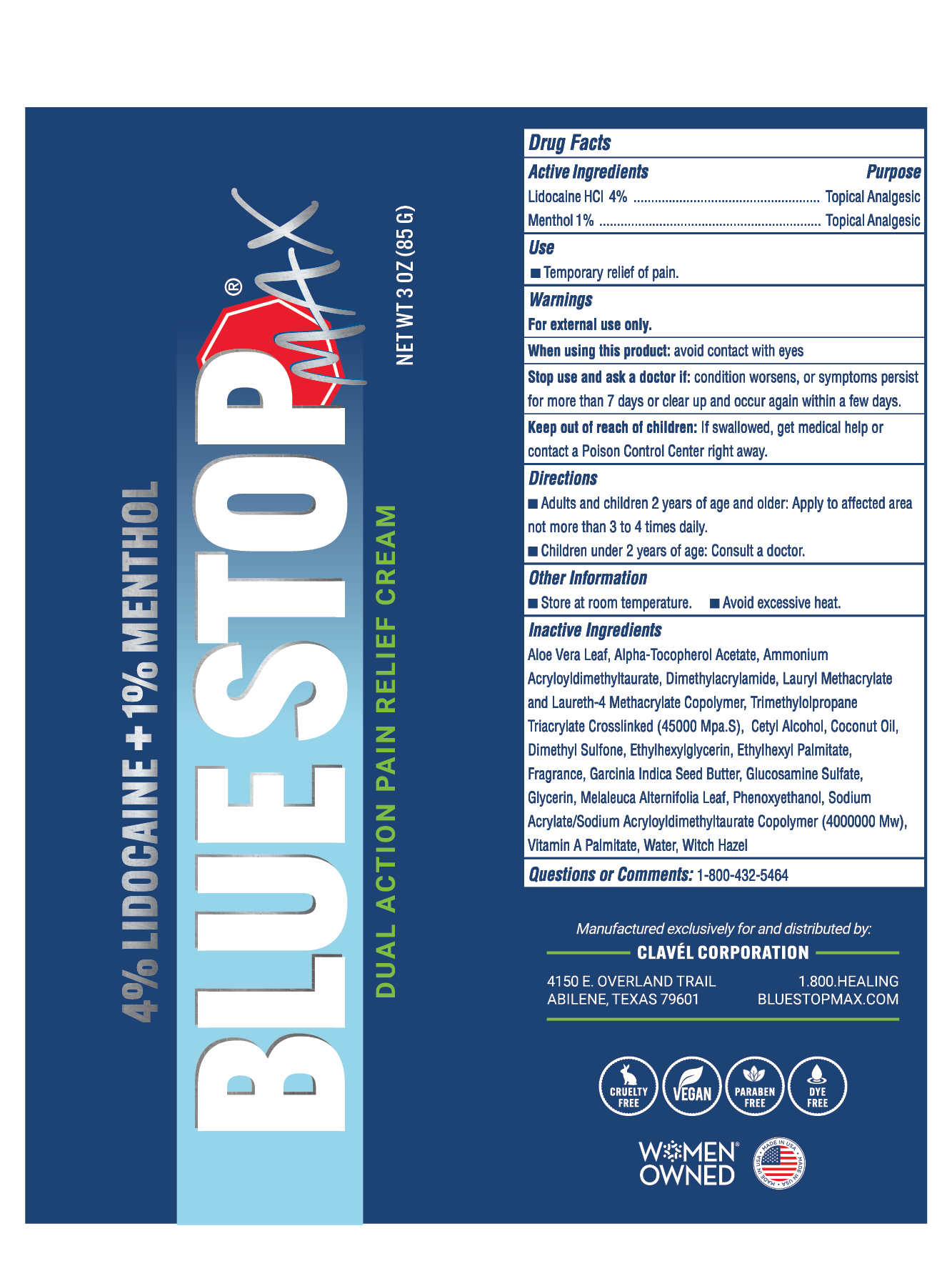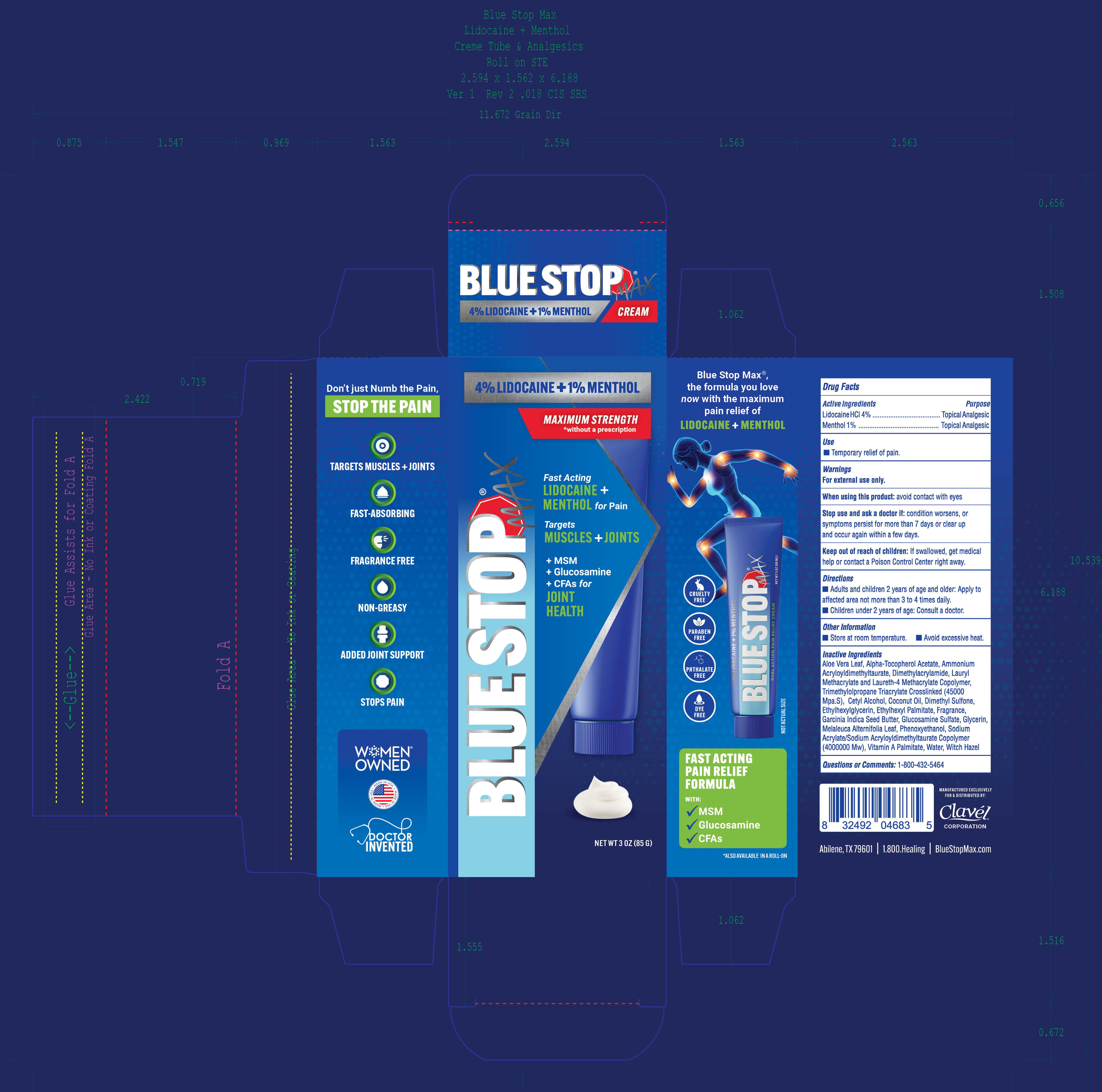 DRUG LABEL: BlueStop Max
NDC: 82714-002 | Form: CREAM
Manufacturer: Clavel Corporation
Category: otc | Type: HUMAN OTC DRUG LABEL
Date: 20260112

ACTIVE INGREDIENTS: LIDOCAINE HYDROCHLORIDE 40 mg/1 g; MENTHOL, (+)- 10 mg/1 g
INACTIVE INGREDIENTS: ALPHA-TOCOPHEROL ACETATE; COCONUT OIL; CETYL ALCOHOL; GLUCOSAMINE SULFATE; ETHYLHEXYL PALMITATE; DIMETHYL SULFONE; MELALEUCA ALTERNIFOLIA LEAF; ALOE VERA LEAF; AMMONIUM ACRYLOYLDIMETHYLTAURATE, DIMETHYLACRYLAMIDE, LAURYL METHACRYLATE AND LAURETH-4 METHACRYLATE COPOLYMER, TRIMETHYLOLPROPANE TRIACRYLATE CROSSLINKED (45000 MPA.S); GLYCERIN; WATER; GARCINIA INDICA SEED BUTTER; WITCH HAZEL; ETHYLHEXYLGLYCERIN; PHENOXYETHANOL; SODIUM ACRYLATE/SODIUM ACRYLOYLDIMETHYLTAURATE COPOLYMER (4000000 MW); VITAMIN A PALMITATE

BlueStop Max Cream

Active Ingredients

Lidocaine HCl 4%

Menthol 1%

Purpose

Topical Analgesic

Use

Temporary relief of pain

Warnings

For external use only

When using this product: avoid contact with the eyes

Stop use and ask a doctor if: condition worsens, or symptoms persist for more than 7 days or clear up and occur again within a few days

Keep out of reach of children. If swallowed, get medical help or contact a Poison Control Center right away.

Directions

- Adults and children 2 years of age and older: Apply to affected area not more than 3 to 4 times daily.
- Children under 2 yeas of age: Consult a doctor

Other Information

- Store at room temperature
- Avoidexcessive heat

Inactive Ingredients

Aloe Vera Leaf, Alpha-Tocopherol Acetate, Ammonium Acryloyldimethyltaurate, Dimethylacrylamide, Lauryl Methacrylate and Laureth-4 Methacrylate Copolymer, Trimethylolpropane Triacrylate Crosslinked (45000 Mpa.S), Cetyl Alcohol, Coconut Oil, Dimethyl Sulfone, Ethylhexylglycerin,Ethylhexyl Palmitate, Fragrance, Garcinia Indica Seed Butter, Glucosamine Sulfate, Glycerin, Melaleuca Alternifolia Leaf, Phenoxyethanol, Sodium Acrylate/Sodium Acryloyldimethyltaurate Copolymer (4000000 MW), Vitamin A Palmitate, Water, Witch Hazel

Questions or Comments?

1-800-432-5464